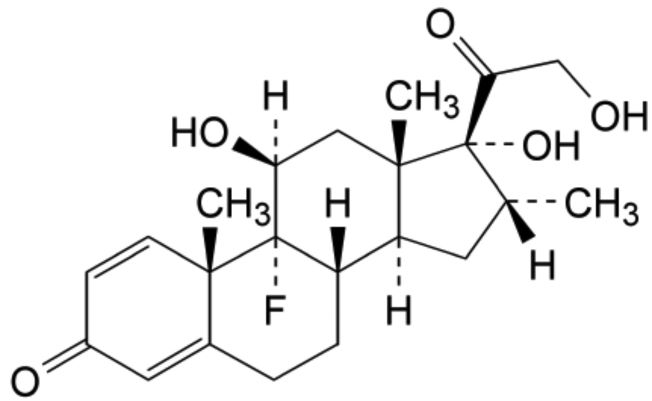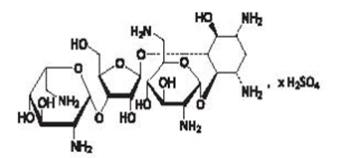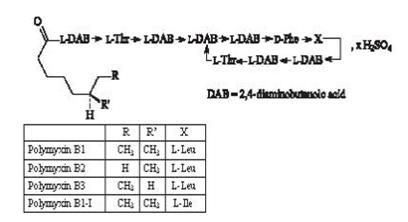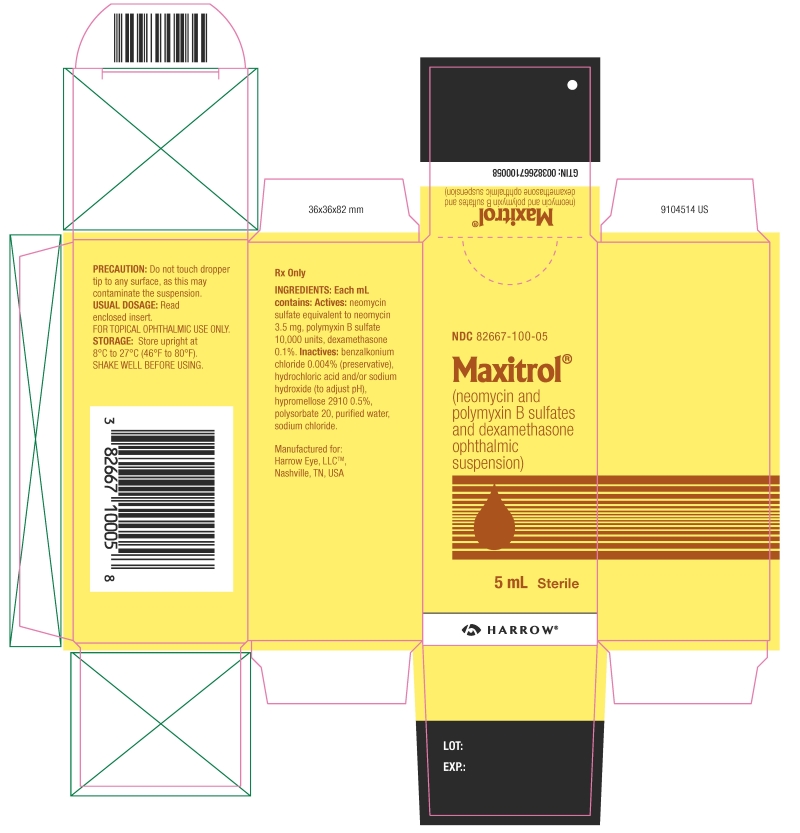 DRUG LABEL: Maxitrol
NDC: 82667-100 | Form: SUSPENSION
Manufacturer: Harrow Eye, LLC
Category: prescription | Type: HUMAN PRESCRIPTION DRUG LABEL
Date: 20251024

ACTIVE INGREDIENTS: NEOMYCIN SULFATE 3.5 mg/1 mL; POLYMYXIN B SULFATE 10000 [USP'U]/1 mL; DEXAMETHASONE 1 mg/1 mL
INACTIVE INGREDIENTS: BENZALKONIUM CHLORIDE; HYPROMELLOSE 2910 (4000 MPA.S); SODIUM CHLORIDE; POLYSORBATE 20; HYDROCHLORIC ACID; SODIUM HYDROXIDE; WATER

MAXITROL- neomycin sulfate, polymyxin b sulfate and dexamethasone suspension

DESCRIPTION

MAXITROL®(neomycin and polymyxin B sulfates and dexamethasone ophthalmic suspension) is a multiple dose anti-infective steroid combination in sterile suspension form for topical application. The chemical structure for the active ingredient, dexamethasone, is:

Molecular Weight = 392.45 g/mol

C 22 H 29 FO 5

Established name: dexamethasone

Chemical name: pregna-1, 4-diene-3, 20-dione, 9-fluoro-11,17, 21-trihydroxy-16-methyl-, (11β, 16α)-.

The other active ingredients are neomycin sulfate and polymyxin B sulfate. The structural formula for neomycin sulfate is:

Neomycin B (R1=H, R2=CH2NH2)

Neomycin C (R1=CH2NH2, R2=H)

The structural formula for polymyxin B sulfate is:

Each mL of MAXITROL®(neomycin and polymyxin B sulfates and dexamethasone ophthalmic suspension) contains: Actives:neomycin sulfate equivalent to neomycin 3.5 mg, polymyxin B sulfate 10,000 units, dexamethasone 0.1%. Inactives:benzalkonium chloride 0.004% (preservative), hydrochloric acid and/or sodium hydroxide (to adjust pH), hypromellose 2910 0.5%, polysorbate 20, purified water, sodium chloride.

CLINICAL PHARMACOLOGY

Corticosteroids suppress the inflammatory response to a variety of agents and they probably delay or slow healing. Since corticosteroids may inhibit the body's defense mechanism against infection, a concomitant antimicrobial drug may be used when this inhibition is considered to be clinically significant in a particular case.

When a decision to administer both a corticosteroid and an antimicrobial is made, the administration of such drugs in combination has the advantage of greater patient compliance and convenience, with the added assurance that the appropriate dosage of both drugs is administered, plus assured compatibility of ingredients when both types of drugs are in the same formulation and, particularly, that the correct volume of drug is delivered and retained.

The relative potency of corticosteroids depends on the molecular structure, concentration and release from the vehicle.

INDICATIONS AND USAGE

For steroid-responsive inflammatory ocular conditions for which a corticosteroid is indicated and where bacterial infection or a risk of bacterial infection exists.

Ocular corticosteroids are indicated in inflammatory conditions of the palpebral and bulbar conjunctiva, cornea, and anterior segment of the globe where the inherent risk of corticosteroids use in certain infective conjunctivitides is accepted to obtain a diminution in edema and inflammation. They are also indicated in chronic anterior uveitis and corneal injury from chemical, radiation or thermal burns; or penetration of foreign bodies.

The use of a combination drug with an anti-infective component is indicated where the risk of infection is high or where there is an expectation that potentially dangerous numbers of bacteria will be present in the eye.

The particular anti-infective drug in this product is active against the following common bacterial eye pathogens: Staphylococcus aureus, Escherichia coli, Haemophilusinfluenzae, Klebsiella/Enterobacterspecies, Neisseriaspecies, and Pseudomonas aeruginosa.

This product does not provide adequate coverage against: Serratia marcescensand S treptococci, including Streptococcus pneumoniae.

CONTRAINDICATIONS

MAXITROL®(neomycin and polymyxin B sulfates and dexamethasone ophthalmic suspension) is contraindicated in most viral diseases of the cornea and conjunctiva, including epithelial herpes simplex keratitis (dendritic keratitis), vaccinia, varicella, and also in mycobacterial infection of the eye and fungal diseases of ocular structures. MAXITROL is also contraindicated in individuals with known or suspected hypersensitivity to any of the ingredients of this preparation and to other corticosteroids.

WARNINGS

NOT FOR INJECTION. Use of ocular steroids may prolong the course and may exacerbate the severity of many viral infections of the eye (including herpes simplex). Employment of a corticosteroid medication in the treatment of patients with a history of herpes simplex requires great caution; frequent slit lamp microscopy is recommended.

Prolonged use of corticosteroids may result in glaucoma with damage to the optic nerve, defects in visual acuity and fields of vision, and in posterior subcapsular cataract formation. Prolonged use may also suppress the host immune response and thus increase the hazard of secondary ocular infections. Acute purulent or parasitic infections of the eye may be masked or activity enhanced by the presence of corticosteroid medication.

Various ocular diseases and long-term use of topical corticosteroids have been known to cause corneal and scleral thinning. Use of topical corticosteroids in the presence of thin corneal or scleral tissue may lead to perforation.

If this product is used for 10 days or longer, intraocular pressure (IOP) should be routinely monitored even though it may be difficult in children and uncooperative patients. Steroids should be used with caution in the presence of glaucoma. IOP should be checked frequently.

The use of steroids after cataract surgery may delay healing and increase the incidence of bleb formation.

MAXITROL®(neomycin and polymyxin B sulfates and dexamethasone ophthalmic suspension) is not for injection. It should never be injected subconjunctivally, nor should it be directly introduced into the anterior chamber of the eye.

Products containing neomycin sulfate may cause cutaneous sensitization. Sensitivity to topically administered aminoglycosides, such as neomycin, may occur in some patients. Severity of hypersensitivity reactions may vary from local effects to generalized reactions such as erythema, itching, urticaria, skin rash, anaphylaxis, anaphylactoid reactions, or bullous reactions. If hypersensitivity develops during use of the product, treatment should be discontinued. Cross-hypersensitivity to other aminoglycosides can occur, and the possibility that patients who become sensitized to topical neomycin may also be sensitive to other topical and/or systemic aminoglycosides should be considered.

PRECAUTIONS

General

The initial prescription and renewal of the medication order beyond 20 mL of MAXITROL®(neomycin and polymyxin B sulfates and dexamethasone ophthalmic suspension) should be made by a physician only after examination of the patient with the aid of magnification, such as slit lamp biomicroscopy, and where appropriate, fluorescein staining. If signs and symptoms fail to improve after two days, the patient should be reevaluated.

As fungal infections of the cornea are particularly prone to develop coincidentally with long-term corticosteroid applications, fungal invasion should be suspected in any persistent corneal ulceration where a corticosteroid has been used or is in use. Fungal cultures should be taken when appropriate.

If this product is used for 10 days or longer, IOP should be monitored (see WARNINGS).

Prolonged use of topical anti-bacterial agents may give rise to overgrowth of non-susceptible organisms including fungi.

Information for Patients

If inflammation or pain persists longer than 48 hours or becomes aggravated, the patient should be advised to discontinue use of the medication and consult a physician.

This product is sterile when packaged. To prevent contamination, care should be taken to avoid touching the bottle tip to eyelids or to any other surface. The use of this bottle by more than one person may spread infection. Keep bottle tightly closed when not in use. Keep out of reach of children.

Patients should be advised that their vision may be temporarily blurred following dosing with MAXITROL®(neomycin and polymyxin B sulfates and dexamethasone ophthalmic suspension). Care should be exercised in operating machinery or driving a motor vehicle.

Carcinogenesis, Mutagenesis, Impairment of Fertility

Long-term studies in animals to evaluate carcinogenic or mutagenic potential have not been conducted with polymyxin B sulfate. Treatment of cultured human lymphocytes in vitro with neomycin increased the frequency of chromosome aberrations at the highest concentration (80 mcg/mL) tested. However, the effects of neomycin on carcinogenesis and mutagenesis in humans are unknown. Polymyxin B has been reported to impair the motility of equine sperm, but its effects on male or female fertility are unknown.

Pregnancy

Dexamethasone has been shown to be teratogenic in mice and rabbits following topical ophthalmic application in multiples of the therapeutic dose.

In the mouse, corticosteroids produce fetal resorptions and a specific abnormality, cleft palate. In the rabbit, corticosteroids have produced fetal resorptions and multiple abnormalities involving the head, ears, limbs, palate, etc.

There are no adequate or well-controlled studies in pregnant women. However, prolonged or repeated corticoid use during pregnancy has been associated with an increased risk of intra-uterine growth retardation. MAXITROL®(neomycin and polymyxin B sulfates and dexamethasone ophthalmic suspension) should be used during pregnancy only if the potential benefit to the mother justifies the potential risk to the embryo or fetus. Infants born of mothers who have received substantial doses of corticosteroids during pregnancy should be observed carefully for signs of hypoadrenalism.

Nursing Mothers

Systemically administered corticosteroids appear in human milk, could suppress growth, interfere with endogenous corticosteroid production, or cause other untoward effects. It is not known whether topical administration of corticosteroids could result in sufficient systemic absorption to produce detectable quantities in human milk. Because many drugs are excreted in human milk, caution should be exercised when MAXITROL®(neomycin and polymyxin B sulfates and dexamethasone ophthalmic suspension) is administered to a nursing woman.

Pediatric Use

Safety and effectiveness in pediatric patients below the age of 2 years have not been established.

Geriatric Use

No overall differences in safety or effectiveness have been observed between elderly and younger patients.

ADVERSE REACTIONS

Adverse reactions have occurred with corticosteroid/anti-infective combination drugs which can be attributed to the corticosteroid component, the anti-infective component, or the combination. Exact incidence figures are not available since no denominator of treated patients is available.

Reactions occurring most often from the presence of the anti-infective ingredient are allergic sensitizations. The reactions due to the corticosteroid component are: elevation of IOP with possible development of glaucoma, and infrequent optic nerve damage; posterior subcapsular cataract formation; and delayed wound healing. Corticosteroid-containing preparations have also been reported to cause perforation of the globe. Keratitis, conjunctivitis, corneal ulcers, and conjunctival hyperemia have occasionally been reported following use of steroids.

Additional adverse reactions identified from post marketing use include ulcerative keratitis, headache, and Stevens-Johnson syndrome.

The following additional adverse reactions have been reported with dexamethasone use:

Cushing’s syndrome and adrenal suppression may occur after use of dexamethasone in excess of the listed dosing instructions in predisposed patients, including children and patients treated with CYP3A4 inhibitors.

DOSAGE AND ADMINISTRATION

One to two drops in the conjunctival sac(s). In severe disease, drops may be used hourly, being tapered to discontinuation as the inflammation subsides. In mild disease, drops may be used up to four to six times daily. Not more than 20 mL should be prescribed initially, and the prescription should not be refilled without further evaluation as outlined in PRECAUTIONS above.

HOW SUPPLIED

MAXITROL®(neomycin and polymyxin B sulfates and dexamethasone ophthalmic suspension) is supplied as a sterile ophthalmic suspension in a white, low density polyethylene dispenser with a pink, polypropylene cap as follows:

5 mL in 8 mL bottle………………………………………………………. NDC82667-100-05

Storage: Store upright at 8°C to 27°C (46°F to 80°F).

After opening, MAXITROL®(neomycin and polymyxin B sulfates and dexamethasone ophthalmic suspension) can be used until the expiration date on the bottle.

Harrow®

Manufactured for:

Harrow Eye, LLC™

Nashville, TN, USA

Revised: September 2024

PRINCIPAL DISPLAY PANEL

NDC 82667-100-05

Maxitrol®

(neomycin and

polymyxin B sulfates

and dexamethasone

ophthalmic

suspension)

5 mL Sterile

HARROW®